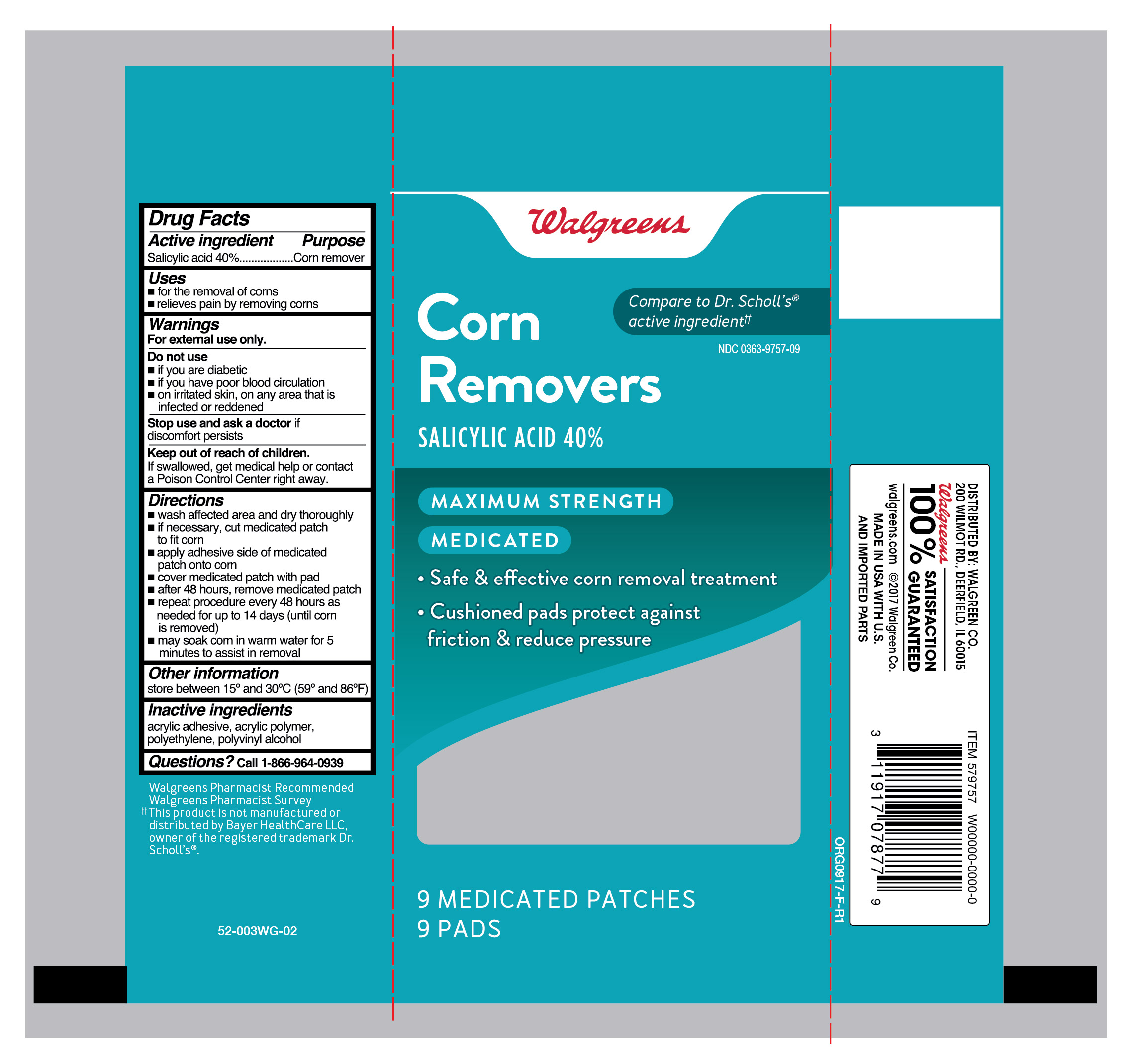 DRUG LABEL: Salicylic Acid
NDC: 0363-9757 | Form: PATCH
Manufacturer: Walgreen Company
Category: otc | Type: HUMAN OTC DRUG LABEL
Date: 20260120

ACTIVE INGREDIENTS: SALICYLIC ACID 40 mg/9 1
INACTIVE INGREDIENTS: POLYVINYL ALCOHOL; HIGH DENSITY POLYETHYLENE

Walgreens Medicated Corn Removers

Active ingredient

Salicylic acid 40%

Purpose

Corn remover

Uses

- for the removal of corns
- relieves pain by removing corns

Warnings

For external use only.

Do not use

- if you are diabetic
- if you have poor blood circulation
- on irritated skin, on any area that is infected or reddened

Stop use and ask a doctor

If discomfort persists

Keep out of reach of children.

If swallowed, get medical help or contact a Poison Control Center right away.

Directions

- wash affected area and dry thoroughly
- if necessary, cut medicated patch to fit corn
- apply adhesive side down of medicated patch onto corn
- cover medicated patch with pad
- after 48 hours, remove medicated patch
- repeat procedure every 48 hours as needed for up to 14 days (until corn is removed)
- may soak corn in warm water for 5 minutes to assist in removal

Other information

store between 15°C to 30°C (59°F to 86°F)

Inactive ingredients

acrylic adhesive, acrylic polymer, polyethylene, polyvinyl alcohol

Questions?

call 1-866-964-0939

Principal Display Panel

Walgreens

Corn

Removers

SALICYLIC ACID 40%

MAXIMUM STRENGTH

MEDICATED

- Safe & effective corn removal treatment
- Cushioned pads protect against friction & reduced pressure

9 MEDICATED PATCHES

9 PADS